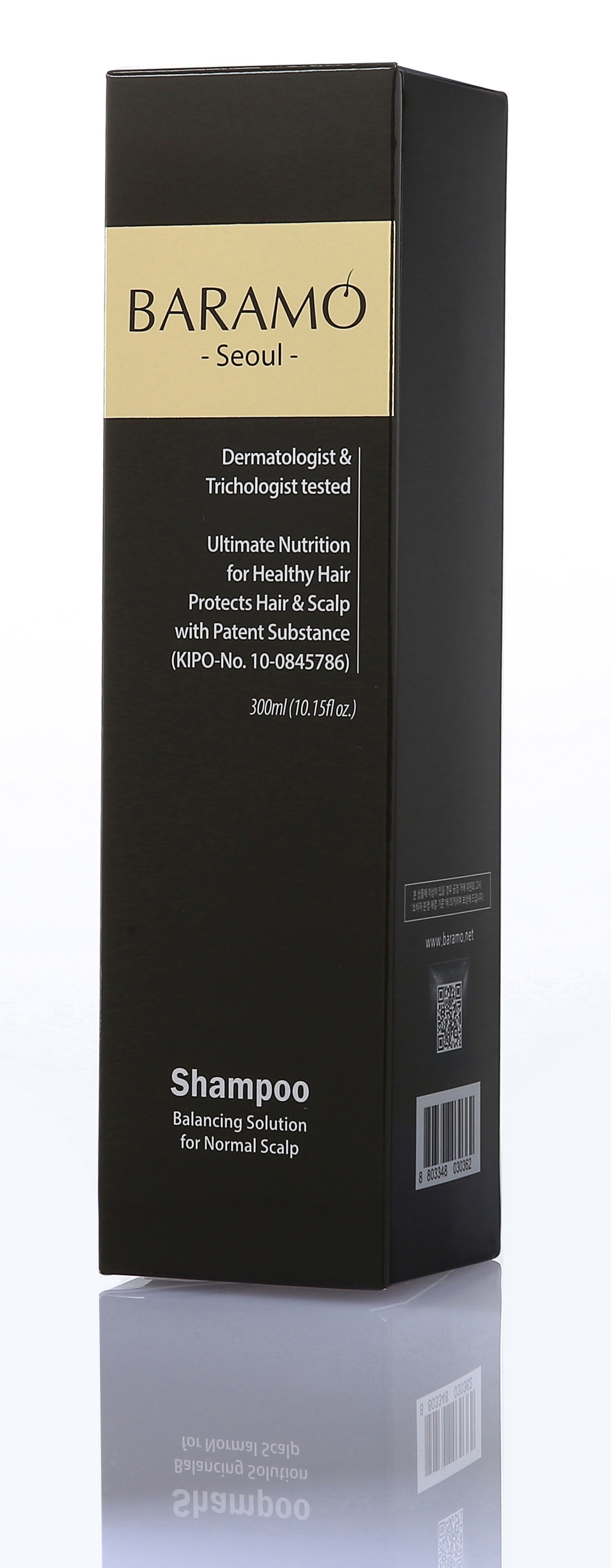 DRUG LABEL: BARAMO for Normal Scalp
NDC: 69961-030 | Form: SHAMPOO
Manufacturer: Mentor Lab
Category: otc | Type: HUMAN OTC DRUG LABEL
Date: 20161024

ACTIVE INGREDIENTS: STYPHNOLOBIUM JAPONICUM FLOWER BUD 0.10 g/300 mL
INACTIVE INGREDIENTS: Water; Cocamidopropyl Betaine

ACTIVE INGREDIENT

Active Ingredient: Sophora Japonica Bud Extract 0.035%

INACTIVE INGREDIENT

Inactive Ingredients: Water, Cocamidopropyl Betaine, Potassium Cocoyl Glycinate, Glycerin, Sodium Lauroyl Sarcosinate, Coco-glucoside, Propylene Glycol Laurate, Sodium Cocoyl Alaninate, Sodium Chloride, PEG-60 Hydrogenated Castor Oil, Polysorbate 20, PEG-150 Distearate, PEG-120 Methyl Glucose Dioleate, Sodium Benzoate, Hydroxyethyl Urea, PEG-150 Pentaerythrityl Tetrastearate, Fragrance, Citric Acid, Polyquaternium-10, Propanediol, Menthol, Disodium EDTA, Sophora Japonica Bud Extract, Sophora Flavescens Root Extract, Rosmarinus Officinalis (Rosemary) Leaf Extract, Punica Granatum Fruit Extract, Polygonum Multiflorum Root Extract, Panax Ginseng Root Extract, Glycyrrhiza Glabra (Licorice) Root Extract, Glycine Soja (Soybean) Seed Extract, Eriobotrya Japonica Leaf Extract, Coptis Japonica Root Extract, Citrus Paradisi (Grapefruit) Fruit Extract, Citrus Limon (Lemon) Fruit Extract, Camellia Sinensis Leaf Extract, Anemarrhena Asphodeloides Root Extract.

PURPOSE

Purpose: purifies & nourishes hair and scalp

WARNINGS

Warnings: 1. Stop using the product if the following problems arise while using the product as continued use could worsen the symptoms; consult with a dermatologist. 2. Do not use on areas with wounds, eczema, and dermatitis. 3. Storage and handling precautions. 4. Wash off the product if it gets in the eye. 5. Inadequate cleansing after use could lead to bleaching; cleanse adequately after use. 6. Keep out of reach of children. 7. Store in a cool, dry place away from direct sunlight. 8. External use only.

KEEP OUT OF REACH OF CHILDREN

Direction

Direction: -For best use, use BARAMO shampoo daily in night. It helps your scalp keep clean and get healthy through the night. -Apply to wet hair & gently massage into a gentle & rich lather. -Leave gentle & rich lather on your hair about 2-3 minutes. -Rinse thoroughly with warm water. -Condition your hair with BARAMO Hair Conditioner for silky hair

Direction

Direction: -For best use, use BARAMO shampoo daily in night. It helps your scalp keep clean and get healthy through the night. -Apply to wet hair & gently massage into a gentle & rich lather. -Leave gentle & rich lather on your hair about 2-3 minutes. -Rinse thoroughly with warm water. -Condition your hair with BARAMO Hair Conditioner for silky hair